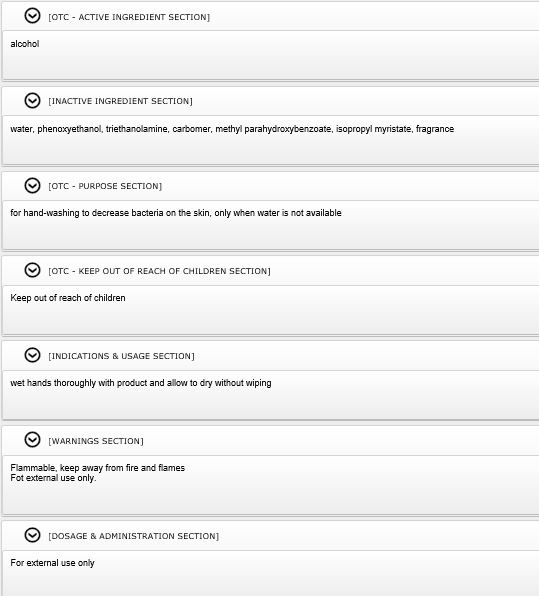 DRUG LABEL: Puredot hand sanitizer
NDC: 77929-0002 | Form: GEL
Manufacturer: IKYNY MEDIA Co.,Ltd.
Category: otc | Type: HUMAN OTC DRUG LABEL
Date: 20200527

ACTIVE INGREDIENTS: ALCOHOL 70 mL/100 mL
INACTIVE INGREDIENTS: METHYLPARABEN; ISOPROPYL MYRISTATE; WATER; PHENOXYETHANOL; GREEN TEA LEAF; CARBOMER 934; TROLAMINE

ACTIVE INGREDIENT

alcohol

INACTIVE INGREDIENT

water, phenoxyethanol, triethanolamine, carbomer, methyl parahydroxybenzoate, isopropyl myristate, fragrance

PURPOSE

for hand-washing to decrease bacteria on the skin, only when water is not available

Keep out of reach of children

INDICATIONS AND USAGE

wet hands thoroughly with product and allow to dry without wiping

WARNINGS

Flammable, keep away from fire and flames
Fot external use only.

DOSAGE AND ADMINISTRATION

For external use only